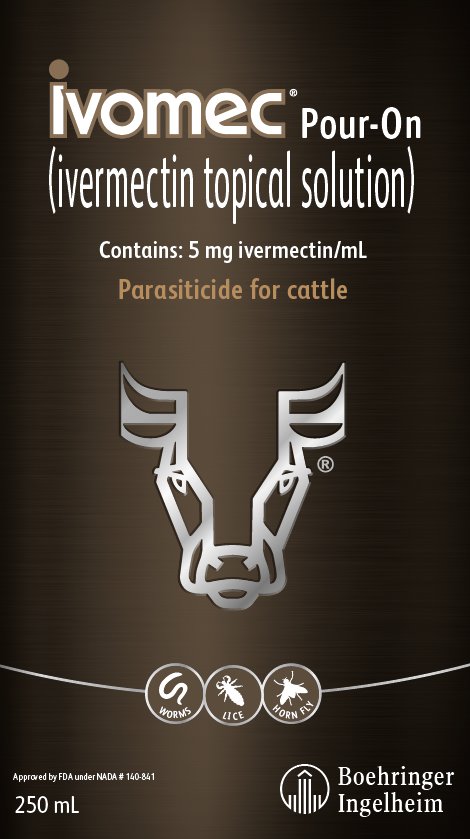 DRUG LABEL: IVOMEC
NDC: 0010-4734 | Form: SOLUTION
Manufacturer: Boehringer Ingelheim Animal Health USA Inc.
Category: animal | Type: OTC ANIMAL DRUG LABEL
Date: 20240718

ACTIVE INGREDIENTS: ivermectin 5 mg/1 mL

Ivomec® Pour-On
(ivermectin topical solution)

Approved by FDA under NADA # 140-841

Parasiticide for cattle

Contains 5 mg ivermectin/mL

Consult your veterinarian for assistance in the diagnosis, treatment and control of parasitism.

INTRODUCTION

IVOMEC® Pour-On (ivermectin topical solution) delivers internal and external parasite control in one convenient low-volume application. Discovered and developed by scientists from Merck Research Laboratories, IVOMEC Pour-On (ivermectin topical solution) contains ivermectin, a unique chemical entity.

MODE OF ACTION

Ivermectin is a member of the macrocylic lactone class of endectocides which have a unique mode of action. Compounds of the class bind selectively and with high affinity to glutamate-gated chloride ion channels which occur in invertebrate nerve and muscle cells.

This leads to an increase in the permeability of the cell membrane to chloride ions with hyperpolarization of the nerve or muscle cell, resulting in paralysis and death of the parasite. Compounds of this class may also interact with other ligand-gated chloride channels, such as those gated by the neurotransmitter gamma-aminobutyric acid (GABA).

The margin of safety for compounds of this class is attributable to the fact that mammals do not have glutamate-gated chloride channels, the macrocyclic lactones have a low affinity for other mammalian ligand-gated chloride channels and they do not readily cross the blood-brain barrier.

INDICATIONS

IVOMEC Pour-On (ivermectin topical solution) applied at the recommended dose level of 500 mcg/kg is indicated for the effective treatment and control of these parasites.

Gastrointestinal Roundworms
Ostertagia ostertagi (including inhibited stage) | (adults and L4)
Haemonchus placei | (adults and L4)
Trichostrongylus axei | (adults and L4)
T. colubriformis | (adults and L4)
Cooperia oncophora | (adults and L4)
Cooperia punctata | (adults and L4)
Cooperia surnabada | (adults and L4)
Strongyloides papillosus | (adults)
Oesophagostomum radiatum | (adults and L4)
Trichuris spp. | (adults)
Lungworms
Dictyocaulus viviparus | (adults and L4)
Cattle Grubs | (parasitic stages)
Hypoderma bovis
H. Iineatum
Mites
Sarcoptes scabiei var. bovis
Lice
Linognathus vituli
Haematopinus eurysternus
Damalinia bovis
Solenopotes capillatus
Horn Flies
Haematobia irritans

PERSISTENT ACTIVITY

IVOMEC Pour-On (ivermectin topical solution) has been proved to effectively control infections and to protect cattle from re-infection with: Oesophagostomum radiatum and Dictyocaulus viviparus for 28 days after treatment; Cooperia punctata and Trichostrongylus axei for 21 days after treatment; Ostertagia ostertagi, Haemonchus placei, Cooperia oncophora and Cooperia surnabada for 14 days after treatment; Damalinia bovis for 56 days after treatment.

TREATMENT OF CATTLE FOR HORN FLIES

IVOMEC Pour-On (ivermectin topical solution) controls horn flies (Haematobia irritans) for up to 28 days after dosing. For best results IVOMEC Pour-On (ivermectin topical solution) should be part of a parasite control program for both internal and external parasites based on the epidemiology of these parasites. Consult your veterinarian or an entomologist for the most effective timing of applications.

DOSAGE

The dose rate is 1 mL for each 22 lb of body weight. The formulation should be applied along the topline in a narrow strip extending from the withers to the tailhead.

Do not underdose. Ensure each animal receives a complete dose based on a current body weight. Underdosing may result in ineffective treatment, and encourage the development of parasite resistance.

ADMINISTRATION

Metering Cup with Measure-Squeeze-Pour System (250 mL Container with 25 mL Metering Cup and 1 Liter Container with 60 mL Metering Cup)

This pack contains 1 Metering Cup and 1 dip tube

1. Insert the dip tube into base of the Metering Cup. Leave the "slotted end" of the dip tube exposed in the bottom of the container.
2. Unscrew shipping cap from container top.
3. Screw the Metering Cup onto container top.
4. Measure: To select the correct dose rate, rotate the adjuster cap (top) in either direction to position the dose indicator to the weight of the animal you want to treat. When body weight is between markings, use the higher setting.
5. Squeeze the container gently to fill the Metering Cup to the required dose. Release your grip and any excess will return to the container.
6. Pour: Apply the full dose by tipping and pouring along the backline of the animal until the Metering Cup is empty.
7. Storage: The Metering Cup should not remain attached to the container when not in use. Detach the Metering Cup after each use and replace the shipping cap to close the container top.

Collapsible Pack
(2.5 L Pack and 5 L Pack)

Connect the applicator gun to the collapsible pack as follows:

- Attach the open end of the draw-off tubing to the dosing equipment. (Because of the solvents used in the formulation, only the Protector Drench Gun from Instrument Supplies Limited, or equivalent, is recommended. Other applicators may exhibit compatibility problems resulting in locking, incorrect dosage or leakage.)
- Replace the shipping cap with the draw-off cap and tighten down. Attach draw-off tubing to the draw-off cap.
- Gently prime the applicator gun, checking for leaks.
- Follow the manufacturer's directions for adjusting the dose.
- When the interval between uses of the applicator gun is expected to exceed 12 hours, disconnect the gun and draw-off tubing from the product container and empty the product from the gun and tubing back into the product container. To prevent removal of special lubricants from the Protector Drench Gun, the gun and tubing must not be washed.

20 Liter Pack

Use dosing equipment (applicator, draw-off tubing, cap with stem) compatible with IVOMEC Pour-On (ivermectin topical solution). Other dosing equipment may be incompatible, resulting in locking, incorrect dosage and leakage. Follow the dosing equipment manufacturer's directions for adjusting the dose and proper use and maintenance of the dosing equipment. Connect the dosing applicator and the draw-off tubing to the container as follows:

- Attach the open end of the draw-off tubing to an appropriate dosing applicator. Attach draw-off tubing to the cap with the stem. Replace the shipping cap with the cap having the draw-off tubing. Gently prime the dosing applicator, checking for leaks.
- When the interval between uses of the applicator gun is expected to exceed 12 hours, disconnect the gun, draw-off tubing and cap with stem from the product container, empty the product from the gun and tubing back into the product container and replace the shipping cap.

ANIMAL SAFETY

Studies conducted in the U.S.A. have demonstrated the safety margin for ivermectin. Based on plasma levels, the topically applied formulation is expected to be at least as well tolerated by breeding animals as is the subcutaneous formulation which had no effect on breeding performance.

WARNING

NOT FOR USE IN HUMANS.
Keep this and all drugs out of the reach of children.

The Safety Data Sheet (SDS) contains more detailed occupational safety information. To report suspected adverse drug events, for technical assistance, or to obtain a copy of the Safety Data Sheet (SDS), contact Boehringer Ingelheim Animal Health USA Inc. at 1-888-637-4251.

WARNING! FLAMMABLE!
KEEP AWAY FROM HEAT, SPARKS, OPEN FLAME, AND OTHER SOURCES OF IGNITION.

This product should not be applied to self or others because it may be irritating to human skin and eyes and absorbed through the skin. To minimize accidental skin contact, the user should wear a long-sleeved shirt and rubber gloves. If accidental skin contact occurs, wash immediately with soap and water. If accidental eye exposure occurs, flush eyes immediately with water and seek medical attention.

RESIDUE WARNING

Cattle must not be treated within 48 days of slaughter for human consumption. Because a withdrawal time in milk has not been established, do not use in female dairy cattle of breeding age. A withdrawal period has not been established for this product in pre-ruminating calves. Do not use in calves to be processed for veal.

PRECAUTIONS

- Store at or below 25°C (77°F) and protect from light. Excursions permitted to 104°F (40°C).
- Use only in well-ventilated areas or outdoors.
- Close container tightly when not in use.
- Cattle should not be treated when hair or hide is wet since reduced efficacy may be experienced.
- Do not use when rain is expected to wet cattle within six hours after treatment.
- This product is for application to skin surface only. Do not give orally or parenterally.
- Cloudiness in the formulation may occur when IVOMEC® Pour-On is stored at temperatures below 32°F. Allowing to warm at room temperature will restore the normal appearance without affecting efficacy.
- Antiparasitic activity of ivermectin will be impaired if the formulation is applied to areas of the skin with mange scabs or lesions, or with dermatoses or adherent materials, e.g., caked mud or manure.
- Ivermectin has been associated with adverse reactions in sensitive dogs; therefore, IVOMEC Pour-On (ivermectin topical solution) is not recommended for use in species other than cattle.
- Restricted Drug (California) - Use only as directed.

When to Treat Cattle with Grubs

IVOMEC Pour-On (ivermectin topical solution) effectively controls all stages of cattle grubs. However, proper timing of treatment is important. For the most effective results, cattle should be treated as soon as possible after the end of the heel fly (warble fly) season. While this is not peculiar to ivermectin, destruction of Hypoderma larvae (cattle grubs) at the period when these grubs are in vital areas may cause undesirable host-parasite reactions. Killing Hypoderma lineatum when it is in the esophageal tissues may cause bloat; killing H. bovis when it is in the vertebral canal may cause staggering or paralysis. Cattle should be treated either before or after these stages of grub development.

Cattle treated with IVOMEC Pour-On (ivermectin topical solution) at the end of the fly season may be re-treated with IVOMEC during the winter without danger of grub-related reactions. For further information and advice on a planned parasite control program, consult your veterinarian.

OTHER WARNINGS:

Parasite resistance may develop to any dewormer, and has been reported for most classes of dewormers.

Treatment with a dewormer used in conjunction with parasite management practices appropriate to the geographic area and the animal(s) to be treated may slow the development of parasite resistance.

Fecal examinations or other diagnostic tests and parasite management history should be used to determine if the product is appropriate for the herd, prior to the use of any dewormer. Following the use of any dewormer, effectiveness of treatment should be monitored (for example, with the use of a fecal egg count reduction test or another appropriate method).

A decrease in a drug’s effectiveness over time as calculated by fecal egg count reduction tests may indicate the development of resistance to the dewormer administered. Your parasite management plan should be adjusted accordingly based on regular monitoring.

Environmental Safety

Studies indicate that when ivermectin comes in contact with soil it readily and tightly binds to the soil and becomes inactive over time. Free ivermectin may adversely affect fish and certain aquatic organisms. Do not permit cattle to enter lakes, streams or ponds for at least six hours after treatment. Do not contaminate water by direct application or by improper disposal of drug containers. Dispose of containers in an approved landfill or by incineration.

As with other avermectins, ivermectin is excreted in the dung of treated animals and can inhibit the reproduction and growth of pest and beneficial insects that use dung as a source of food and for reproduction. The magnitude and duration of such effects are species and life-cycle specific. When used according to label directions, the product is not expected to have an adverse impact on populations of dung-dependent insects.

How Supplied

IVOMEC Pour-On (ivermectin topical solution) is available in an 250 mL bottle or 1 L bottle with a measure-squeeze-pour system, or in an 2.5 L or 5 L collapsible pack, or 20 L container intended for use with appropriate automatic dosing equipment.

Marketed by:

Boehringer Ingelheim Animal Health USA Inc.

Duluth, GA 30096

Origin China

IVOMEC® and Cattle Head Logo are registered trademarks of Boehringer Ingelheim Animal Health USA Inc.

© 2023 Boehringer Ingelheim Animal Health USA Inc. All rights reserved.

Rev. 03-2023
1050-1445-09